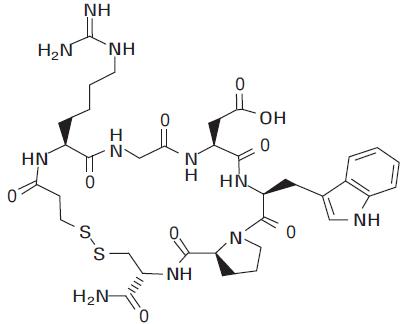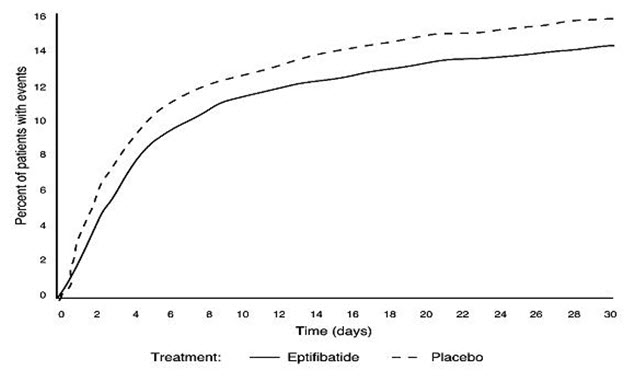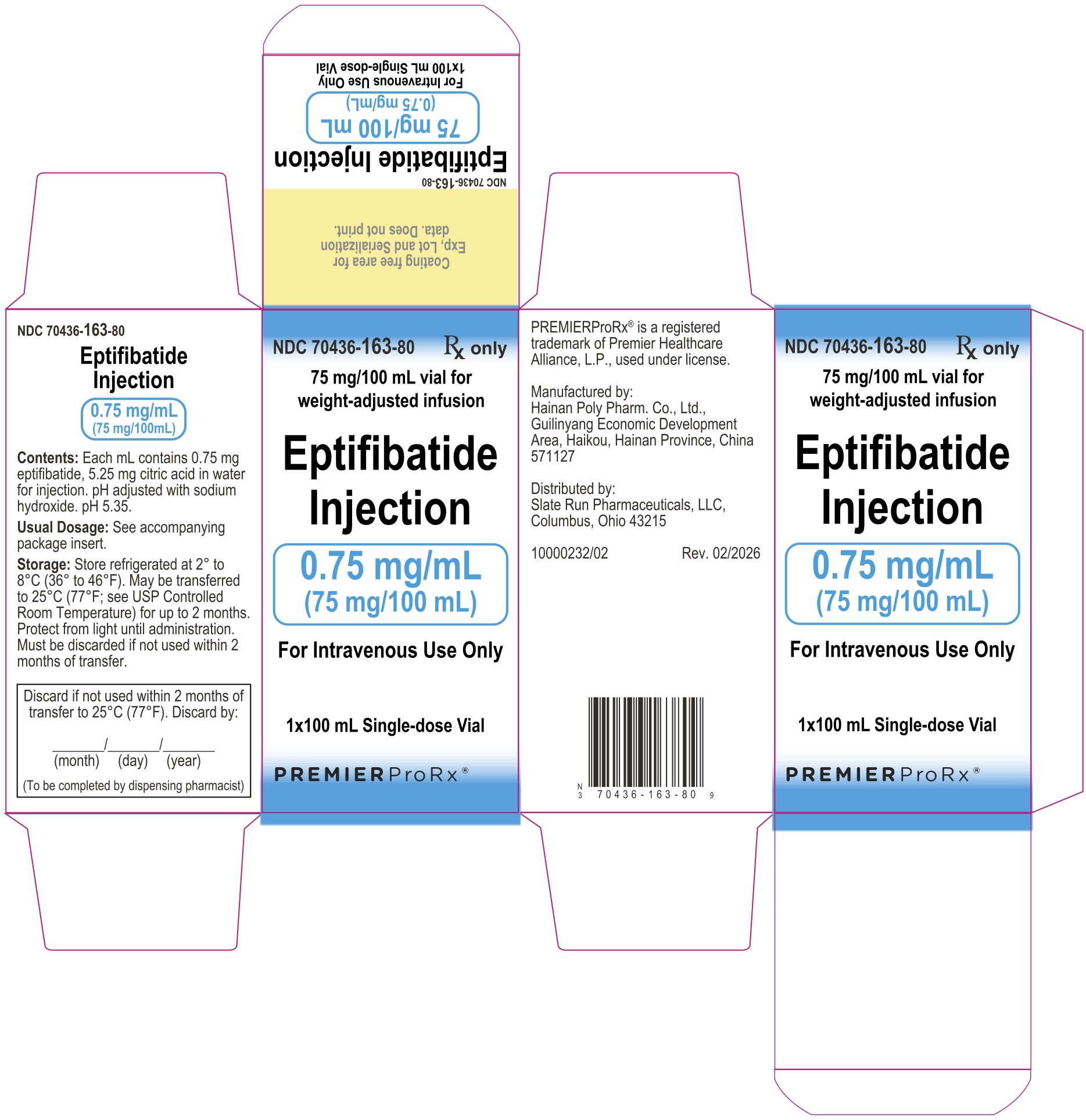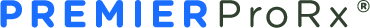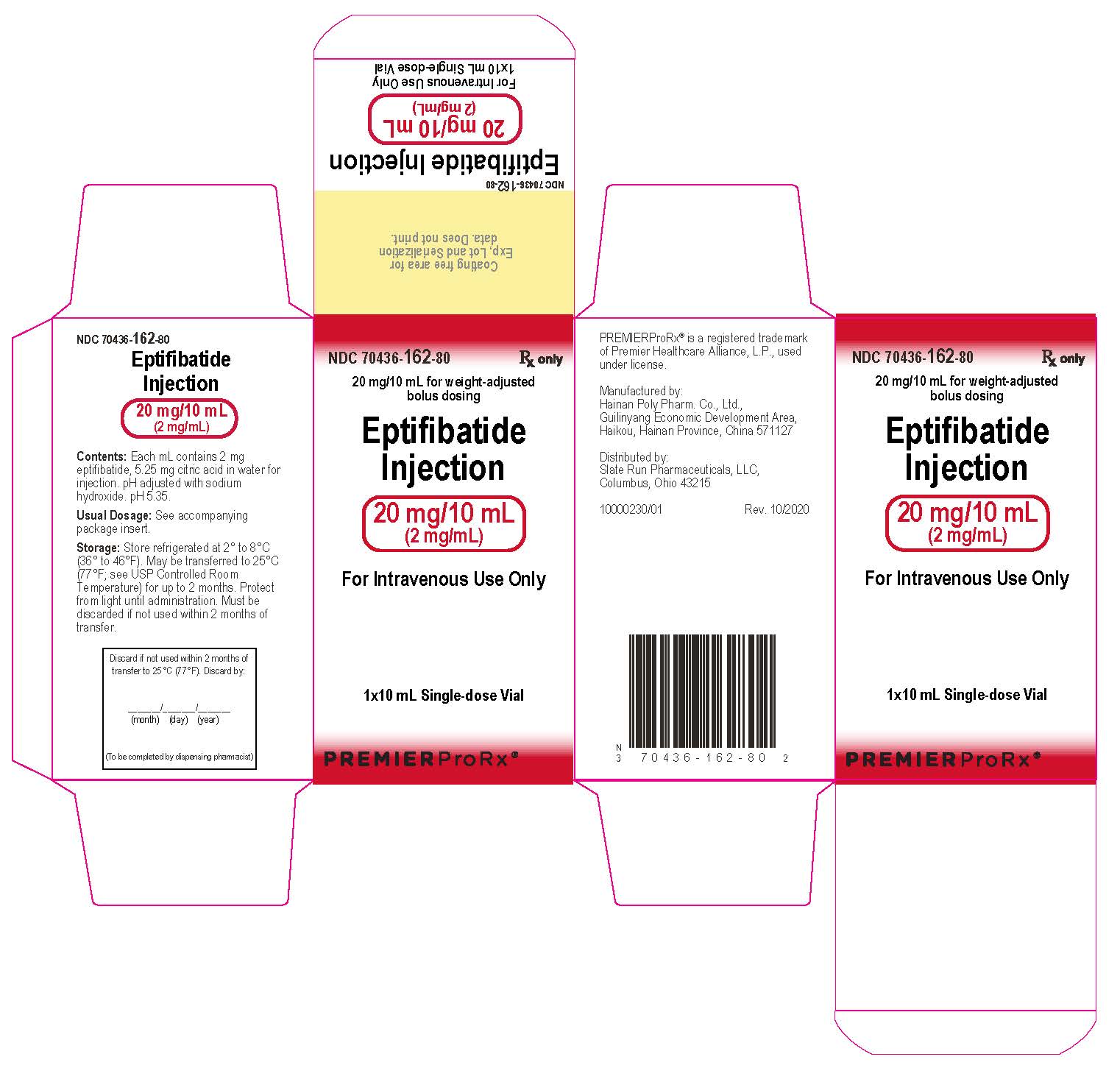 DRUG LABEL: Eptifibatide
NDC: 70436-162 | Form: INJECTION
Manufacturer: Slate Run Pharmaceuticals, LLC
Category: prescription | Type: HUMAN PRESCRIPTION DRUG LABEL
Date: 20260209

ACTIVE INGREDIENTS: EPTIFIBATIDE 2 mg/1 mL
INACTIVE INGREDIENTS: CITRIC ACID MONOHYDRATE; SODIUM HYDROXIDE

HIGHLIGHTS OF PRESCRIBING INFORMATION

These highlights do not include all the information needed to use EPTIFIBATIDE INJECTION safely and effectively. See full prescribing information for EPTIFIBATIDE INJECTION.
EPTIFIBATIDE injection, for intravenous use
Initial U.S. Approval: 1998

1 INDICATIONS AND USAGE

Eptifibatide injection is a platelet aggregation inhibitor indicated for:

- Treatment of acute coronary syndrome (ACS) managed medically or with percutaneous coronary intervention (PCI). (1.1)
- Treatment of patients undergoing PCI (including intracoronary stenting) (1.2)

2 DOSAGE AND ADMINISTRATION

ACS or PCI: 180 mcg/kg IV bolus as soon as possible after diagnosis followed by infusion at 2 mcg/kg/min. (2.1, 2.2)

PCI: Add a second 180 mcg/kg bolus at 10 minutes. (2.2)

In patients with creatinine clearance less than 50 mL/min, reduce the infusion to 1 mcg/kg/min. (2.1, 2.2, 2.3)

3 DOSAGE FORMS AND STRENGTHS

- 20 mg/10 mL (2 mg/mL) in a single-dose vial for bolus injection. (3)
- 75 mg/100 mL (0.75 mg/mL) in a single-dose vial for infusion. (3)

4 CONTRAINDICATIONS

- Bleeding diathesis or bleeding within the previous 30 days. (4)
- Severe uncontrolled hypertension. (4)
- Major surgery within the preceding 6 weeks. (4)
- Stroke within 30 days or any history of hemorrhagic stroke. (4)
- Coadministration of another parenteral GP IIb/IIIa inhibitor. (4)
- Dependency on renal dialysis. (4)
- Known hypersensitivity to any component of the product. (4)

5 WARNINGS AND PRECAUTIONS

- Eptifibatide injection can cause serious bleeding. If bleeding cannot be controlled, discontinue eptifibatide injection immediately. Minimize vascular and other traumas. If heparin is given concomitantly, monitor aPTT or ACT. (5.1)
- Thrombocytopenia: Discontinue eptifibatide injection and heparin. Monitor and treat condition appropriately. (5.2)

6 ADVERSE REACTIONS

Bleeding and hypotension are the most commonly reported adverse reactions. (6.1)

To report SUSPECTED ADVERSE REACTIONS, contact Slate Run Pharmaceuticals, LLC at 1-888-341-9214 or FDA at 1-800-FDA-1088 or www.fda.gov/medwatch.

7 DRUG INTERACTIONS

- Coadministration of antiplatelet agents, thrombolytics, heparin, aspirin, and chronic NSAID use increases the risk of bleeding. Avoid concomitant use with other glycoprotein (GP) IIb/IIIa inhibitors. (7.1)

8 USE IN SPECIFIC POPULATIONS

- Geriatric Use:Risk of bleeding increases with age. (8.5)

FULL PRESCRIBING INFORMATION

1 INDICATIONS AND USAGE

1.1 Acute Coronary Syndrome (ACS)

Eptifibatide injection is indicated to decrease the rate of a combined endpoint of death or new myocardial infarction (MI) in patients with ACS (unstable angina [UA]/non-ST-elevation myocardial infarction [NSTEMI]), including patients who are to be managed medically and those undergoing percutaneous coronary intervention (PCI).

1.2 Percutaneous Coronary Intervention (PCI)

Eptifibatide injection is indicated to decrease the rate of a combined endpoint of death, new MI, or need for urgent intervention in patients undergoing PCI, including those undergoing intracoronary stenting [see Clinical Studies (14.1, 14.2)] .

2 DOSAGE AND ADMINISTRATION

Before infusion of eptifibatide injection, the following laboratory tests should be performed to identify pre-existing hemostatic abnormalities: hematocrit or hemoglobin, platelet count, serum creatinine, and PT/aPTT. In patients undergoing PCI, the activated clotting time (ACT) should also be measured.

The activated partial thromboplastin time (aPTT) should be maintained between 50 and 70 seconds unless PCI is to be performed. In patients treated with heparin, bleeding can be minimized by close monitoring of the aPTT and ACT.

2.1 Dosage in Acute Coronary Syndrome (ACS)

Indication | Normal Renal Function | Creatinine Clearance less than 50 mL/min
Patients with ACS | 180 mcg/kg intravenous (IV) bolus as soon as possible after diagnosis, followed by continuous infusion of 2 mcg/kg/min | 180 mcg/kg IV bolus as soon as possible after diagnosis, followed by continuous infusion of 1 mcg/kg/min
 | - Infusion should continue until hospital discharge or initiation of coronary artery bypass graft surgery (CABG), up to 72 hours. - If a patient is to undergo PCI, the infusion should be continued until hospital discharge or for up to 18 to 24 hours after the procedure, whichever comes first, allowing for up to 96 hours of therapy. - Aspirin, 160 to 325 mg, should be given daily.

Eptifibatide injection should be given concomitantly with heparin dosed to achieve the following parameters:

During Medical Management: Target aPTT 50 to 70 seconds

- If weight greater than or equal to 70 kg, 5000-unit bolus followed by infusion of 1000 units/h.
- If weight less than 70 kg, 60-units/kg bolus followed by infusion of 12 units/kg/h.

During PCI: Target ACT 200 to 300 seconds

- If heparin is initiated prior to PCI, additional boluses during PCI to maintain an ACT target of 200 to 300 seconds.
- Heparin infusion after the PCI is discouraged.

2.2 Dosage in Percutaneous Coronary Intervention (PCI)

Indication | Normal Renal Function | Creatinine Clearance less than 50 mL/min
Patients with PCI | 180 mcg/kg IV bolus immediately before PCI followed by continuous infusion of; 2 mcg/kg/min and a second bolus of; 180 mcg/kg (given 10 minutes after the first bolus) | 180 mcg/kg IV bolus immediately before PCI followed by continuous infusion of; 1 mcg/kg/min and a second bolus of; 180 mcg/kg (given 10 minutes after the first bolus)
 | - Infusion should be continued until hospital discharge, or for up to 18 to 24 hours, whichever comes first. A minimum of 12 hours of infusion is recommended. - In patients who undergo CABG surgery, eptifibatide infusion should be discontinued prior to surgery. - Aspirin, 160 to 325 mg, should be given 1 to 24 hours prior to PCI and daily thereafter.

- Eptifibatide injection should be given concomitantly with heparin to achieve a target ACT of 200 to 300 seconds. Administer 60-units/kg bolus initially in patients not treated with heparin within 6 hours prior to PCI.
- Additional boluses during PCI to maintain ACT within target.
- Heparin infusion after the PCI is strongly discouraged.

Patients requiring thrombolytic therapy should discontinue eptifibatide injection.

2.3 Important Administration Instructions

1. Inspect eptifibatide injection for particulate matter and discoloration prior to administration, whenever solution and container permit.
2. May administer eptifibatide injection in the same intravenous line as alteplase, atropine, dobutamine, heparin, lidocaine, meperidine, metoprolol, midazolam, morphine, nitroglycerin, or verapamil. Do not administer eptifibatide injection through the same intravenous line as furosemide.
3. May administer eptifibatide injection in the same IV line with 0.9% NaCl or 0.9% NaCl/5% dextrose. With either vehicle, the infusion may also contain up to 60 mEq/L of potassium chloride.
4. Withdraw the bolus dose(s) of eptifibatide injection from the 10 mL vial into a syringe. Administer the bolus dose(s) by IV push.
5. Immediately following the bolus dose administration, initiate a continuous infusion of eptifibatide injection. When using an intravenous infusion pump, administer eptifibatide injection undiluted directly from the 100-mL vial. Spike the 100 mL vial with a vented infusion set. Center the spike within the circle on the stopper top.
6. Discard any unused portion left in the vial.

Administer eptifibatide injection by volume according to patient weight (see Table 1).

Table 1. Eptifibatide Injection Dosing Charts by Weight
Patient Weight |  | 180 mcg/kg Bolus Volume | 2 mcg/kg/min Infusion Volume (CrCl greater than or equal to 50 mL/min) |  | 1 mcg/kg/min Infusion Volume (CrCl less than 50 mL/min)
(kg) | (lb) | (from 2 mg/mL vial) | (from; 2 mg/mL; 100 mL vial) | (from; 0.75 mg/mL 100 mL vial) | (from; 2 mg/mL; 100 mL vial) | (from; 0.75 mg/mL 100 mL vial)
37-41 | 81-91 | 3.4 mL | 2 mL/h | 6 mL/h | 1 mL/h | 3 mL/h
42-46 | 92-102 | 4 mL | 2.5 mL/h | 7 mL/h | 1.3 mL/h | 3.5 mL/h
47-53 | 103-117 | 4.5 mL | 3 mL/h | 8 mL/h | 1.5 mL/h | 4 mL/h
54-59 | 118-130 | 5 mL | 3.5 mL/h | 9 mL/h | 1.8 mL/h | 4.5 mL/h
60-65 | 131-143 | 5.6 mL | 3.8 mL/h | 10 mL/h | 1.9 mL/h | 5 mL/h
66-71 | 144-157 | 6.2 mL | 4 mL/h | 11 mL/h | 2 mL/h | 5.5 mL/h
72-78 | 158-172 | 6.8 mL | 4.5 mL/h | 12 mL/h | 2.3 mL/h | 6 mL/h
79-84 | 173-185 | 7.3 mL | 5 mL/h | 13 mL/h | 2.5 mL/h | 6.5 mL/h
85-90 | 186-198 | 7.9 mL | 5.3 mL/h | 14 mL/h | 2.7 mL/h | 7 mL/h
91-96 | 199-212 | 8.5 mL | 5.6 mL/h | 15 mL/h | 2.8 mL/h | 7.5 mL/h
97-103 | 213-227 | 9 mL | 6 mL/h | 16 mL/h | 3.0 mL/h | 8 mL/h
104-109 | 228-240 | 9.5 mL | 6.4 mL/h | 17 mL/h | 3.2 mL/h | 8.5 mL/h
110-115 | 241-253 | 10.2 mL | 6.8 mL/h | 18 mL/h | 3.4 mL/h | 9 mL/h
116-121 | 254-267 | 10.7 mL | 7 mL/h | 19 mL/h | 3.5 mL/h | 9.5 mL/h
>121 | >267 | 11.3 mL | 7.5 mL/h | 20 mL/h | 3.7 mL/h | 10 mL/h

3 DOSAGE FORMS AND STRENGTHS

- Injection: 20 mg of eptifibatide injection in 10 mL (2 mg/mL), for intravenous bolus.
- Injection: 75 mg of eptifibatide injection in 100 mL (0.75 mg/mL), for intravenous infusion.

4 CONTRAINDICATIONS

Treatment with eptifibatide injection is contraindicated in patients with:

- A history of bleeding diathesis, or evidence of active abnormal bleeding within the previous 30 days
- Severe hypertension (systolic blood pressure >200 mm Hg or diastolic blood pressure >110 mm Hg) not adequately controlled on antihypertensive therapy
- Major surgery within the preceding 6 weeks
- History of stroke within 30 days or any history of hemorrhagic stroke
- Current or planned administration of another parenteral GP IIb/IIIa inhibitor
- Dependency on renal dialysis
- Hypersensitivity to eptifibatide injection or any component of the product (hypersensitivity reactions that occurred included anaphylaxis and urticaria).

5 WARNINGS AND PRECAUTIONS

5.1 Bleeding

Bleeding is the most common complication encountered during eptifibatide injection therapy. Administration of eptifibatide injection is associated with an increase in major and minor bleeding, as classified by the criteria of the Thrombolysis in Myocardial Infarction Study group (TIMI) [see Adverse Reactions (6.1)] . Most major bleeding associated with eptifibatide injection has been at the arterial access site for cardiac catheterization or from the gastrointestinal or genitourinary tract. Minimize the use of arterial and venous punctures, intramuscular injections, and the use of urinary catheters, nasotracheal intubation, and nasogastric tubes. When obtaining intravenous access, avoid non-compressible sites (e.g., subclavian or jugular veins).

Use of Thrombolytics, Anticoagulants, and Other Antiplatelet Agents

Risk factors for bleeding include older age, a history of bleeding disorders, and concomitant use of drugs that increase the risk of bleeding (thrombolytics, oral anticoagulants, nonsteroidal anti-inflammatory drugs, and P2Y12inhibitors). Concomitant treatment with other inhibitors of platelet receptor glycoprotein (GP) IIb/IIIa should be avoided. In patients treated with heparin, bleeding can be minimized by close monitoring of the aPTT and ACT [see Dosage and Administration (2)] .

Care of the Femoral Artery Access Site in Patients Undergoing Percutaneous Coronary Intervention (PCI)

In patients undergoing PCI, treatment with eptifibatide injection is associated with an increase in major and minor bleeding at the site of arterial sheath placement. After PCI, eptifibatide infusion should be continued until hospital discharge or up to 18 to 24 hours, whichever comes first. Heparin use is discouraged after the PCI procedure. Early sheath removal is encouraged while eptifibatide injection is being infused. Prior to removing the sheath, it is recommended that heparin be discontinued for 3 to 4 hours and an aPTT of <45 seconds or ACT <150 seconds be achieved. In any case, both heparin and eptifibatide injection should be discontinued and sheath hemostasis should be achieved at least 2 to 4 hours before hospital discharge. If bleeding at access site cannot be controlled with pressure, infusion of eptifibatide injection and heparin should be discontinued immediately.

5.2 Thrombocytopenia

There have been reports of acute, profound thrombocytopenia (immune-mediated and non-immune mediated) with eptifibatide injection. In the event of acute profound thrombocytopenia or a confirmed platelet decrease to <100,000/mm^3, discontinue eptifibatide injection and heparin (unfractionated or low-molecular weight). Monitor serial platelet counts, assess the presence of drug-dependent antibodies, and treat as appropriate [see Adverse Reactions (6.1)] .

There has been no clinical experience with eptifibatide injection initiated in patients with a baseline platelet count <100,000/mm^3. If a patient with low platelet counts is receiving eptifibatide injection, their platelet count should be monitored closely.

6 ADVERSE REACTIONS

The following serious adverse reaction is also discussed elsewhere in the labeling:

- Bleeding [see Contraindications (4) and Warnings and Precautions (5.1)]

6.1 Clinical Trials Experience

Because clinical studies are conducted under widely varying conditions, adverse reaction rates observed in the clinical studies of a drug cannot be directly compared to rates in the clinical trials of another drug and may not reflect the rates observed in clinical practice.

A total of 16,782 patients were treated in the Phase III clinical trials (PURSUIT, ESPRIT, and IMPACT II) [see Clinical Studies (14)] . These 16,782 patients had a mean age of 62 years (range: 20-94 years). Eighty-nine percent of the patients were Caucasian, with the remainder being predominantly Black (5%) and Hispanic (5%). Sixty-eight percent were men. Because of the different regimens used in PURSUIT, IMPACT II, and ESPRIT, data from the 3 studies were not pooled.

Bleeding and hypotension were the most commonly reported adverse reactions (incidence ≥5% and greater than placebo) in the eptifibatide injection controlled clinical trial database.

Bleeding

The incidence of bleeding and transfusions in the PURSUIT and ESPRIT studies are shown in Table 2. Bleeding was classified as major or minor by the criteria of the TIMI study group. Major bleeding consisted of intracranial hemorrhage and other bleeding that led to decreases in hemoglobin greater than 5 g/dL. Minor bleeding included spontaneous gross hematuria, spontaneous hematemesis, other observed blood loss with a hemoglobin decrease of more than 3 g/dL, and other hemoglobin decreases that were greater than 4 g/dL but less than 5 g/dL. In patients who received transfusions, the corresponding loss in hemoglobin was estimated through an adaptation of the method of Landefeld et al.

Table 2. Bleeding and Transfusions in the PURSUIT and ESPRIT Studies
PURSUIT (ACS)
 | Placebo; n (%) | EptifibatideInjection; 180/2; n (%)
Patients | 4696 | 4679
Major bleeding* | 425 (9.3%) | 498 (10.8%)
Minor bleeding* | 347 (7.6%) | 604 (13.1%)
Requiring transfusions† | 490 (10.4%) | 601 (12.8%)
ESPRIT (PCI)
 | Placebo; n (%) | EptifibatideInjection; 180/2/180; n (%)
Patients | 1024 | 1040
Major bleeding* | 4 (0.4%) | 13 (1.3%)
Minor bleeding* | 18 (2%) | 29 (3%)
Requiring transfusions† | 11 (1.1%) | 16 (1.5%)
Note: Denominator is based on patients for whom data are available.
* For major and minor bleeding, patients are counted only once according to the most severe classification.
† Includes transfusions of whole blood, packed red blood cells, fresh frozen plasma, cryoprecipitate, platelets, and autotransfusion during the initial hospitalization.

The majority of major bleeding reactions in the ESPRIT study occurred at the vascular access site (1 and 8 patients, or 0.1% and 0.8% in the placebo and eptifibatide injection groups, respectively). Bleeding at “other” locations occurred in 0.2% and 0.4% of patients, respectively.

In the PURSUIT study, the greatest increase in major bleeding in eptifibatide-treated patients compared to placebo-treated patients was also associated with bleeding at the femoral artery access site (2.8% versus 1.3%). Oropharyngeal (primarily gingival), genitourinary, gastrointestinal, and retroperitoneal bleeding were also seen more commonly in eptifibatide-treated patients compared to placebo-treated patients.

Among patients experiencing a major bleed in the IMPACT II study, an increase in bleeding on eptifibatide injection versus placebo was observed only for the femoral artery access site (3.2% versus 2.8%).

Table 3displays the incidence of TIMI major bleeding according to the cardiac procedures carried out in the PURSUIT study. The most common bleeding complications were related to cardiac revascularization (CABG-related or femoral artery access site bleeding). A corresponding table for ESPRIT is not presented, as every patient underwent PCI in the ESPRIT study and only 11 patients underwent CABG.

Table 3. Major Bleeding by Procedures in the PURSUIT Study
 | Placebo; n (%) | EptifibatideInjection; 180/2; n (%)
Patients | 4577 | 4604
Overall incidence of major bleeding | 425 (9.3%) | 498 (10.8%)
Breakdown by procedure:
CABG | 375 (8.2%) | 377 (8.2%)
Angioplasty without CABG | 27 (0.6%) | 64 (1.4%)
Angiography without angioplasty or CABG | 11 (0.2%) | 29 (0.6%)
Medical therapy only | 12 (0.3%) | 28 (0.6%)
Note: Denominators are based on the total number of patients whose TIMI classification was resolved.

In the PURSUIT and ESPRIT studies, the risk of major bleeding with eptifibatide injection increased as patient weight decreased. This relationship was most apparent for patients weighing less than 70 kg.

Bleeding resulting in discontinuation of the study drug was more frequent among patients receiving eptifibatide injection than placebo (4.6% versus 0.9% in ESPRIT, 8% versus 1% in PURSUIT, 3.5% versus 1.9% in IMPACT II).

Intracranial Hemorrhage and Stroke

Intracranial hemorrhage was rare in the PURSUIT, IMPACT II, and ESPRIT clinical studies. In the PURSUIT study, 3 patients in the placebo group, 1 patient in the group treated with eptifibatide injection 180/1.3, and 5 patients in the group treated with eptifibatide injection 180/2 experienced a hemorrhagic stroke. The overall incidence of stroke was 0.5% in patients receiving eptifibatide injection 180/1.3, 0.7% in patients receiving eptifibatide injection 180/2, and 0.8% in placebo patients.

In the IMPACT II study, intracranial hemorrhage was experienced by 1 patient treated with eptifibatide injection 135/0.5, 2 patients treated with eptifibatide injection 135/0.75, and 2 patients in the placebo group. The overall incidence of stroke was 0.5% in patients receiving 135/0.5 eptifibatide injection, 0.7% in patients receiving eptifibatide injection 135/0.75, and 0.7% in the placebo group.

In the ESPRIT study, there were 3 hemorrhagic strokes, 1 in the placebo group and 2 in the eptifibatide injection group. In addition there was 1 case of cerebral infarction in the eptifibatide injection group.

Immunogenicity/Thrombocytopenia

The potential for development of antibodies to eptifibatide has been studied in 433 subjects. Eptifibatide injection was nonantigenic in 412 patients receiving a single administration of eptifibatide injection (135 mcg/kg bolus followed by a continuous infusion of either 0.5 mcg/kg/min or 0.75 mcg/kg/min), and in 21 subjects to whom eptifibatide injection (135 mcg/kg bolus followed by a continuous infusion of 0.75 mcg/kg/min) was administered twice, 28 days apart. In both cases, plasma for antibody detection was collected approximately 30 days after each dose. The development of antibodies to eptifibatide at higher doses has not been evaluated.

In patients with suspected eptifibatide-related immune-mediated thrombocytopenia, IgG antibodies that react with the GP IIb/IIIa complex were identified in the presence of eptifibatide and in eptifibatide-naïve patients. These findings suggest acute thrombocytopenia after the administration of eptifibatide injection can develop as a result of naturally occurring drug-dependent antibodies or those induced by prior exposure to eptifibatide injection. Similar antibodies were identified with other GP IIb/IIIa ligand-mimetic agents. Immune-mediated thrombocytopenia with eptifibatide injection may be associated with hypotension and/or other signs of hypersensitivity.

In the PURSUIT and IMPACT II studies, the incidence of thrombocytopenia (<100,000/mm^3or ≥50% reduction from baseline) and the incidence of platelet transfusions were similar between patients treated with eptifibatide injection and placebo. In the ESPRIT study, the incidence was 0.6% in the placebo group and 1.2% in the eptifibatide injection group.

Other Adverse Reactions

In the PURSUIT and ESPRIT studies, the incidence of serious nonbleeding adverse reactions was similar in patients receiving placebo or eptifibatide injection (19% and 19%, respectively, in PURSUIT; 6% and 7%, respectively, in ESPRIT). In PURSUIT, the only serious nonbleeding adverse reaction that occurred at a rate of at least 1% and was more common with eptifibatide injection than placebo (7% versus 6%) was hypotension. Most of the serious nonbleeding adverse reactions consisted of cardiovascular reactions typical of a UA population. In the IMPACT II study, serious nonbleeding adverse reactions that occurred in greater than 1% of patients were uncommon and similar in incidence between placebo- and eptifibatide-treated patients.

Discontinuation of study drug due to adverse reactions other than bleeding was uncommon in the PURSUIT, IMPACT II, and ESPRIT studies, with no single reaction occurring in >0.5% of the study population (except for “other” in the ESPRIT study).

6.2 Postmarketing Experience

The following adverse reactions have been reported in post-approval use of eptifibatide injection in combination with heparin and aspirin. Because the reactions below are reported voluntarily from a population of uncertain size, it is generally not possible to reliably estimate their frequency or establish a causal relationship to drug exposure: cerebral, GI, and pulmonary hemorrhage. Fatal bleeding reactions have been reported. Acute profound thrombocytopenia, as well as immune-mediated thrombocytopenia, have been reported [see Adverse Reactions (6.1)] .

7 DRUG INTERACTIONS

7.1 Use of Thrombolytics, Anticoagulants, and Other Antiplatelet Agents

Coadministration of antiplatelet agents, thrombolytics, heparin, aspirin, and chronic NSAID use increases the risk of bleeding. Concomitant treatment with other inhibitors of platelet receptor GP IIb/IIIa should be avoided.

8 USE IN SPECIFIC POPULATIONS

8.1 Pregnancy

Risk Summary

Available data on eptifibatide use in pregnant women from published literature and the pharmacovigilance database are insufficient to establish a drug-associated risk of major birth defects, miscarriage or adverse maternal or fetal outcomes. Untreated myocardial infarction can be fatal to the pregnant woman and fetus [see Clinical Considerations] . In animal reproduction studies, there was no evidence of adverse developmental effects when eptifibatide was administered intravenously to pregnant rats and rabbits at approximately 4 times the recommended maximum daily human dose.

The estimated background risk of major birth defects and miscarriage for the indicated population is unknown. All pregnancies have a background risk of birth defect, loss, or other adverse outcomes. In the U.S. general population, the estimated background risk of major birth defects and miscarriage in clinically recognized pregnancies is 2 to 4% and 15 to 20%, respectively.

Clinical Considerations

Disease-associated maternal and/or embryo/fetal risk:Myocardial infarction is a medical emergency in pregnancy which can be fatal to the pregnant woman and fetus if left untreated. Therapy for the pregnant woman should not be withheld because of potential concerns regarding the effects of eptifibatide injection on the fetus.

Data

Animal Data:Embryo-fetal development studies have been performed by continuous intravenous infusion of eptifibatide in pregnant rats during the period of organogenesis at total daily doses of up to 72 mg/kg/day (about 4 times the recommended maximum daily human dose on a body surface area basis) and in pregnant rabbits during the period of organogenesis at total daily doses of up to 36 mg/kg/day (also about 4 times the recommended maximum daily human dose on a body surface area basis). These studies revealed no evidence of harm to the fetus due to eptifibatide.

8.2 Lactation

Risk Summary

There are no available data on the presence of eptifibatide in human milk, the effects on the breastfed infant, or the effects on milk production. As eptifibatide is a peptide, it is likely to be destroyed in the infant’s gastrointestinal tract and not absorbed orally by the breastfed infant.

8.4 Pediatric Use

Safety and effectiveness of eptifibatide injection in pediatric patients have not been studied.

8.5 Geriatric Use

The PURSUIT and IMPACT II clinical studies enrolled patients up to the age of 94 years (45% were age 65 and over; 12% were age 75 and older). There was no apparent difference in efficacy between older and younger patients treated with eptifibatide injection. The incidence of bleeding complications was higher in the elderly in both placebo and eptifibatide injection groups, and the incremental risk of eptifibatide-associated bleeding was greater in the older patients. No dose adjustment was made for elderly patients, but patients over 75 years of age had to weigh at least 50 kg to be enrolled in the PURSUIT study; no such limitation was stipulated in the ESPRIT study [see Adverse Reactions (6.1)] .

8.6 Renal Impairment

Approximately 50% of eptifibatide is cleared by the kidney in patients with normal renal function. Total drug clearance is decreased by approximately 50% and steady-state plasma eptifibatide injection concentrations are doubled in patients with an estimated CrCl <50 mL/min (using the Cockcroft-Gault equation). Therefore, the infusion dose should be reduced to 1 mcg/kg/min in such patients [see Dosage and Administration (2)] . The safety and efficacy of eptifibatide injection in patients dependent on dialysis has not been established.

10 OVERDOSAGE

There has been only limited experience with overdosage of eptifibatide injection. There were 8 patients in the IMPACT II study, 9 patients in the PURSUIT study, and no patients in the ESPRIT study who received bolus doses and/or infusion doses more than double those called for in the protocols. None of these patients experienced an intracranial bleed or other major bleeding.

Eptifibatide was not lethal to rats, rabbits, or monkeys when administered by continuous intravenous infusion for 90 minutes at a total dose of 45 mg/kg (about 2 to 5 times the recommended maximum daily human dose on a body surface area basis). Symptoms of acute toxicity were loss of righting reflex, dyspnea, ptosis, and decreased muscle tone in rabbits and petechial hemorrhages in the femoral and abdominal areas of monkeys.

From in vitrostudies, eptifibatide is not extensively bound to plasma proteins and thus may be cleared from plasma by dialysis.

11 DESCRIPTION

Eptifibatide is a cyclic heptapeptide containing 6 amino acids and 1 mercaptopropionyl (des-amino cysteinyl) residue. An interchain disulfide bridge is formed between the cysteine amide and the mercaptopropionyl moieties. Chemically it is N^6-(aminoiminomethyl)-N^2-(3-mercapto-1-oxopropyl)-L-lysylglycyl-L-α-aspartyl-L-tryptophyl-L-prolyl-L-cysteinamide, cyclic (1→6)-disulfide. Eptifibatide binds to the platelet receptor glycoprotein (GP) IIb/IIIa of human platelets and inhibits platelet aggregation.

The eptifibatide peptide is produced by solution-phase peptide synthesis, and is purified by preparative reverse-phase liquid chromatography and lyophilized. The structural formula is:

Eptifibatide Injection is a clear, colorless, sterile, non-pyrogenic solution for intravenous (IV) use with an empirical formula of C35H49N11O9S2and a molecular weight of 831.96. Each 10 mL vial contains 2 mg/mL of eptifibatide injection and each 100 mL vial contains 0.75 mg/mL of eptifibatide injection. Each vial of either size also contains 5.25 mg/mL citric acid and sodium hydroxide to adjust the pH to 5.35.

12 CLINICAL PHARMACOLOGY

12.1 Mechanism of Action

Eptifibatide reversibly inhibits platelet aggregation by preventing the binding of fibrinogen, von Willebrand factor, and other adhesive ligands to GP IIb/IIIa. When administered intravenously, eptifibatide inhibits ex vivoplatelet aggregation in a dose- and concentration-dependent manner. Platelet aggregation inhibition is reversible following cessation of the eptifibatide infusion; this is thought to result from dissociation of eptifibatide from the platelet.

12.2 Pharmacodynamics

Infusion of eptifibatide into baboons caused a dose-dependent inhibition of ex vivoplatelet aggregation, with complete inhibition of aggregation achieved at infusion rates greater than 5 mcg/kg/min. In a baboon model that is refractory to aspirin and heparin, doses of eptifibatide that inhibit aggregation prevented acute thrombosis with only a modest prolongation (2- to 3-fold) of the bleeding time. Platelet aggregation in dogs was also inhibited by infusions of eptifibatide, with complete inhibition at 2 mcg/kg/min. This infusion dose completely inhibited canine coronary thrombosis induced by coronary artery injury (Folts model).

Human pharmacodynamic data were obtained in healthy subjects and in patients presenting with UA or NSTEMI and/or undergoing percutaneous coronary intervention. Studies in healthy subjects enrolled only males; patient studies enrolled approximately one-third women. In these studies, eptifibatide injection inhibited ex vivoplatelet aggregation induced by adenosine diphosphate (ADP) and other agonists in a dose- and concentration-dependent manner. The effect of eptifibatide injection was observed immediately after administration of a 180 mcg/kg intravenous bolus. Table 4shows the effects of dosing regimens of eptifibatide injection used in the IMPACT II and PURSUIT studies on ex vivoplatelet aggregation induced by 20 µM ADP in PPACK-anticoagulated platelet-rich plasma and on bleeding time. The effects of the dosing regimen used in ESPRIT on platelet aggregation have not been studied.

Table 4. Platelet Inhibition and Bleeding Time
 | PURSUIT; 180/2*
Inhibition of platelet aggregation 15 min after bolus | 84%
Inhibition of platelet aggregation at steady state | >90%
Bleeding-time prolongation at steady state | <5x
Inhibition of platelet aggregation 4h after infusion discontinuation | <50%
Bleeding-time prolongation 6h after infusion discontinuation | 1.4x
* 180 mcg/kg bolus followed by a continuous infusion of 2 mcg/kg/min.

The eptifibatide injection dosing regimen used in the ESPRIT study included two 180 mcg/kg bolus doses given 10 minutes apart combined with a continuous 2 mcg/kg/min infusion.

When administered alone, eptifibatide injection has no measurable effect on PT or aPTT.

There were no important differences between men and women or between age groups in the pharmacodynamic properties of eptifibatide. Differences among ethnic groups have not been assessed.

12.3 Pharmacokinetics

The pharmacokinetics of eptifibatide are linear and dose-proportional for bolus doses ranging from 90 to 250 mcg/kg and infusion rates from 0.5 to 3 mcg/kg/min. Plasma elimination half-life is approximately 2.5 hours. Administration of a single 180 mcg/kg bolus combined with an infusion produces an early peak level, followed by a small decline prior to attaining steady state (within 4-6 hours). This decline can be prevented by administering a second 180 mcg/kg bolus 10 minutes after the first. The extent of eptifibatide binding to human plasma protein is about 25%. Clearance in patients with coronary artery disease is about 55 mL/kg/h. In healthy subjects, renal clearance accounts for approximately 50% of total body clearance, with the majority of the drug excreted in the urine as eptifibatide, deaminated eptifibatide, and other, more polar metabolites. No major metabolites have been detected in human plasma.

Special Populations

Geriatric

Patients in clinical studies were older (range: 20-94 years) than those in the clinical pharmacology studies. Elderly patients with coronary artery disease demonstrated higher plasma levels and lower total body clearance of eptifibatide when given the same dose as younger patients. Limited data are available on lighter weight (<50 kg) patients over 75 years of age.

Renal Impairment

In patients with moderate to severe renal insufficiency (CrCl <50 mL/min using the Cockcroft-Gault equation), the clearance of eptifibatide is reduced by approximately 50% and steady-state plasma levels approximately doubled [see Use in Specific Populations (8.6) and Dosage and Administration (2)] .

Hepatic Impairment

No studies have been conducted in patients with hepatic impairment.

Gender

Males and females have not demonstrated any clinically significant differences in the pharmacokinetics of eptifibatide.

13 NONCLINICAL TOXICOLOGY

13.1 Carcinogenesis, Mutagenesis, Impairment of Fertility

No long-term studies in animals have been performed to evaluate the carcinogenic potential of eptifibatide. Eptifibatide was not genotoxic in the Ames test, the mouse lymphoma cell (L 5178Y, TK+/-) forward mutation test, the human lymphocyte chromosome aberration test, or the mouse micronucleus test. Administered by continuous intravenous infusion at total daily doses up to 72 mg/kg/day (about 4 times the recommended maximum daily human dose on a body surface area basis), eptifibatide had no effect on fertility and reproductive performance of male and female rats.

14 CLINICAL STUDIES

Eptifibatide injection was studied in 3 placebo-controlled, randomized studies. PURSUIT evaluated patients with acute coronary syndromes: UA or NSTEMI. Two other studies, ESPRIT and IMPACT II, evaluated patients about to undergo a PCI. Patients underwent primarily balloon angioplasty in IMPACT II and intracoronary stent placement, with or without angioplasty, in ESPRIT.

14.1 Non-ST-Segment Elevation Acute Coronary Syndrome

Non-ST-segment elevation acute coronary syndrome is defined as prolonged (≥10 minutes) symptoms of cardiac ischemia within the previous 24 hours associated with either ST-segment changes (elevations between 0.6 mm and 1 mm or depression >0.5 mm), T-wave inversion (>1 mm), or positive CK-MB. This definition includes “unstable angina” and “NSTEMI” but excludes MI that is associated with Q waves or greater degrees of ST-segment elevation.

PURSUIT (Platelet Glycoprotein IIb/IIIa in Unstable Angina: Receptor Suppression Using Eptifibatide Injection Therapy)

PURSUIT was a 726-center, 27-country, double-blind, randomized, placebo-controlled study in 10,948 patients presenting with UA or NSTEMI. Patients could be enrolled only if they had experienced cardiac ischemia at rest (≥10 minutes) within the previous 24 hours and had either ST-segment changes (elevations between 0.6 mm and 1 mm or depression >0.5 mm), T-wave inversion (>1 mm), or increased CK-MB. Important exclusion criteria included a history of bleeding diathesis, evidence of abnormal bleeding within the previous 30 days, uncontrolled hypertension, major surgery within the previous 6 weeks, stroke within the previous 30 days, any history of hemorrhagic stroke, serum creatinine >2 mg/dL, dependency on renal dialysis, or platelet count <100,000/mm^3.

Patients were randomized to placebo, to eptifibatide injection 180 mcg/kg bolus followed by a 2 mcg/kg/min infusion (180/2), or to eptifibatide injection 180 mcg/kg bolus followed by a 1.3 mcg/kg/min infusion (180/1.3). The infusion was continued for 72 hours, until hospital discharge, or until the time of CABG, whichever occurred first, except that if PCI was performed, the eptifibatide infusion was continued for 24 hours after the procedure, allowing for a duration of infusion up to 96 hours.

The lower-infusion-rate arm was stopped after the first interim analysis when the 2 active-treatment arms appeared to have the same incidence of bleeding.

Patient age ranged from 20 to 94 (mean 63) years, and 65% were male. The patients were 89% Caucasian, 6% Hispanic, and 5% Black, recruited in the United States and Canada (40%), Western Europe (39%), Eastern Europe (16%), and Latin America (5%).

This was a “real world” study; each patient was managed according to the usual standards of the investigational site; frequencies of angiography, PCI, and CABG therefore differed widely from site to site and from country to country. Of the patients in PURSUIT, 13% were managed with PCI during drug infusion, of whom 50% received intracoronary stents; 87% were managed medically (without PCI during drug infusion).

The majority of patients received aspirin (75-325 mg once daily). Heparin was administered intravenously or subcutaneously, at the physician's discretion, most commonly as an intravenous bolus of 5000 units followed by a continuous infusion of 1000 units/h. For patients weighing less than 70 kg, the recommended heparin bolus dose was 60 units/kg followed by a continuous infusion of 12 units/kg/h. A target aPTT of 50 to 70 seconds was recommended. A total of 1250 patients underwent PCI within 72 hours after randomization, in which case they received intravenous heparin to maintain an ACT of 300 to 350 seconds.

The primary endpoint of the study was the occurrence of death from any cause or new MI (evaluated by a blinded Clinical Endpoints Committee) within 30 days of randomization.

Compared to placebo, eptifibatide injection administered as a 180 mcg/kg bolus followed by a 2 mcg/kg/min infusion significantly (p=0.042) reduced the incidence of endpoint events (see Table 6). The reduction in the incidence of endpoint events in patients receiving eptifibatide injection was evident early during treatment, and this reduction was maintained through at least 30 days (see Figure 1). Table 5also shows the incidence of the components of the primary endpoint, death (whether or not preceded by an MI) and new MI in surviving patients at 30 days.

Table 5. Clinical Events in the PURSUIT Study
Death or MI | Placebo; (n=4739); n (%) | EptifibatideInjection (180 mcg/kg bolus then 2 mcg/kg/min infusion); (n=4722) n (%) | p-value
3 days | 359 (7.6%) | 279 (5.9%) | 0.001
7 days | 552 (11.6%) | 477 (10.1%) | 0.016
30 days
Death or MI (primary endpoint) | 745 (15.7%) | 672 (14.2%) | 0.042
Death | 177 (3.7%) | 165 (3.5%)
Nonfatal MI | 568 (12%) | 507 (10.7%)

Figure 1. Kaplan-Meier Plot of Time to Death or Myocardial Infarction Within 30 Days of Randomization in the PURSUIT Study

Treatment with eptifibatide injection prior to determination of patient management strategy reduced clinical events regardless of whether patients ultimately underwent diagnostic catheterization, revascularization (i.e., PCI or CABG surgery) or continued to receive medical management alone. Table 6shows the incidence of death or MI within 72 hours.

Table 6. Clinical Events (Death or MI) in the PURSUIT Study Within 72 Hours of Randomization
 | Placebo | EptifibatideInjection; (180 mcg/kg bolus then 2 mcg/kg/min infusion)
Overall patient population | n=4739 | n=4722
– At 72 hours | 7.6% | 5.9%
Patients undergoing early PCI | n=631 | n=619
– Pre-procedure (nonfatal MI only) | 5.5% | 1.8%
– At 72 hours | 14.4% | 9%
Patients not undergoing early PCI | n=4108 | n=4103
– At 72 hours | 6.5% | 5.4%

All of the effect of eptifibatide injection was established within 72 hours (during the period of drug infusion), regardless of management strategy. Moreover, for patients undergoing early PCI, a reduction in events was evident prior to the procedure.

An analysis of the results by sex suggests that women who would not routinely be expected to undergo PCI receive less benefit from eptifibatide injection (95% confidence limits for relative risk of 0.94 - 1.28) than do men (0.72 - 0.9). This difference may be a true treatment difference, the effect of other differences in these subgroups, or a statistical anomaly. No differential outcomes were seen between male and female patients undergoing PCI (see results for ESPRIT).

Follow-up data were available through 165 days for 10,611 patients enrolled in the PURSUIT trial (96.9% of the initial enrollment). This follow-up included 4566 patients who received eptifibatide injection at the 180/2 dose. As reported by the investigators, the occurrence of death from any cause or new MI for patients followed for at least 165 days was reduced from 13.6% with placebo to 12.1% with eptifibatide injection 180/2.

14.2 Percutaneous Coronary Intervention (PCI)

IMPACT II (Eptifibatide Injection to Minimize Platelet Aggregation and Prevent Coronary Thrombosis II)

IMPACT II was a multicenter, double-blind, randomized, placebo-controlled study conducted in the United States in 4010 patients undergoing PCI. Major exclusion criteria included a history of bleeding diathesis, major surgery within 6 weeks of treatment, gastrointestinal bleeding within 30 days, any stroke or structural CNS abnormality, uncontrolled hypertension, PT >1.2 times control, hematocrit <30%, platelet count <100,000/mm^3, and pregnancy.

Patient age ranged from 24 to 89 (mean 60) years, and 75% were male. The patients were 92% Caucasian, 5% Black, and 3% Hispanic. Forty-one percent of the patients underwent PCI for ongoing ACS. Patients were randomly assigned to 1 of 3 treatment regimens, each incorporating a bolus dose initiated immediately prior to PCI followed by a continuous infusion lasting 20 to 24 hours:

1) 135 mcg/kg bolus followed by a continuous infusion of 0.5 mcg/kg/min of eptifibatide injection (135/0.5);

2) 135 mcg/kg bolus followed by a continuous infusion of 0.75 mcg/kg/min of eptifibatide injection (135/0.75); or

3) a matching placebo bolus followed by a matching placebo continuous infusion.

Each patient received aspirin and an intravenous heparin bolus of 100 units/kg, with additional bolus infusions of up to 2000 additional units of heparin every 15 minutes to maintain an ACT of 300 to 350 seconds.

The primary endpoint was the composite of death, MI, or urgent revascularization, analyzed at 30 days after randomization in all patients who received at least 1 dose of study drug.

As shown in Table 7, each eptifibatide injection regimen reduced the rate of death, MI, or urgent intervention, although at 30 days, this finding was statistically significant only in the lower-dose eptifibatide injection group. As in the PURSUIT study, the effects of eptifibatide injection were seen early and persisted throughout the 30-day period.

Table 7. Clinical Events in the IMPACT II Study
 | Placebo n (%) | Eptifibatide Injection (135 mcg/kg bolus then 0.5 mcg/kg/min infusion) n (%) | Eptifibatide Injection (135 mcg/kg bolus then 0.75 mcg/kg/min infusion) n (%)
Patients | 1285 | 1300 | 1286
Abrupt Closure | 65 (5.1%) | 36 (2.8%) | 43 (3.3%)
p-value versus placebo |  | 0.003 | 0.03
Death, MI, or Urgent Intervention
24 hours | 123 (9.6%) | 86 (6.6%) | 89 (6.9%)
p-value versus placebo |  | 0.006 | 0.014
48 hours | 131 (10.2%) | 99 (7.6%) | 102 (7.9%)
p-value versus placebo |  | 0.021 | 0.045
30 days (primary endpoint) | 149 (11.6%) | 118 (9.1%) | 128 (10%)
p-value versus placebo |  | 0.035 | 0.179
Death or MI
30 days | 110 (8.6%) | 89 (6.8%) | 95 (7.4%)
p-value versus placebo |  | 0.102 | 0.272
6 months | 151 (11.9%)* | 136 (10.6%)* | 130 (10.3%)*
p-value versus placebo |  | 0.297 | 0.182
* Kaplan-Meier estimate of event rate.

ESPRIT (Enhanced Suppression of the Platelet IIb/IIIa Receptor with Eptifibatide Injection Therapy)

The ESPRIT study was a multicenter, double-blind, randomized, placebo-controlled study conducted in the United States and Canada that enrolled 2064 patients undergoing elective or urgent PCI with intended intracoronary stent placement. Exclusion criteria included MI within the previous 24 hours, ongoing chest pain, administration of any oral antiplatelet or oral anticoagulant other than aspirin within 30 days of PCI (although loading doses of thienopyridine on the day of PCI were encouraged), planned PCI of a saphenous vein graft or subsequent “staged” PCI, prior stent placement in the target lesion, PCI within the previous 90 days, a history of bleeding diathesis, major surgery within 6 weeks of treatment, gastrointestinal bleeding within 30 days, any stroke or structural CNS abnormality, uncontrolled hypertension, PT >1.2 times control, hematocrit <30%, platelet count <100,000/mm^3, and pregnancy.

Patient age ranged from 24 to 93 (mean 62) years, and 73% of patients were male. The study enrolled 90% Caucasian, 5% African American, 2% Hispanic, and 1% Asian patients. Patients received a wide variety of stents. Patients were randomized either to placebo or eptifibatide injection administered as an intravenous bolus of 180 mcg/kg followed immediately by a continuous infusion of 2 mcg/kg/min, and a second bolus of 180 mcg/kg administered 10 minutes later (180/2/180). Eptifibatide infusion was continued for 18 to 24 hours after PCI or until hospital discharge, whichever came first. Each patient received at least 1 dose of aspirin (162-325 mg) and 60 units/kg of heparin as a bolus (not to exceed 6000 units) if not already receiving a heparin infusion. Additional boluses of heparin (10-40 units/kg) could be administered in order to reach a target ACT between 200 and 300 seconds.

The primary endpoint of the ESPRIT study was the composite of death, MI, urgent target vessel revascularization (UTVR), and “bailout” to open-label eptifibatide injection due to a thrombotic complication of PCI (TBO) (e.g., visible thrombus, “no reflow,” or abrupt closure) at 48 hours. MI, UTVR, and TBO were evaluated by a blinded Clinical Events Committee.

As shown in Table 8, the incidence of the primary endpoint and selected secondary endpoints was significantly reduced in patients who received eptifibatide injection. A treatment benefit in patients who received eptifibatide injection was seen by 48 hours and at the end of the 30-day observation period.

Table 8. Clinical Events in the ESPRIT Study
 | Placebo; (n=1024) | EptifibatideInjection*; (n=1040) | Relative Risk; (95% CI) | p-value
Death, MI, UTVR, or Thrombotic “Bailout”
48 hours (primary endpoint) | 108 (10.5%) | 69 (6.6%) | 0.629 (0.471, 0.84) | 0.0015
30 days | 120 (11.7%) | 78 (7.5%) | 0.64 (0.488, 0.84) | 0.0011
Death, MI, or UTVR
48 hours | 95 (9.3%) | 62 (6%) | 0.643 (0.472, 0.875) | 0.0045
30 days (key secondary endpoint) | 107 (10.4%) | 71 (6.8%) | 0.653 (0.49, 0.871) | 0.0034
Death or MI
48 hours | 94 (9.2%) | 57 (5.5%) | 0.597 (0.435, 0.82) | 0.0013
30 days | 104 (10.2%) | 66 (6.3%) | 0.625 (0.465, 0.84) | 0.0016
* Eptifibatide injection was administered as 180 mcg/kg boluses at times 0 and 10 minutes and an infusion at 2 mcg/kg/min.

The need for thrombotic “bailout” was significantly reduced with eptifibatide injection at 48 hours (2.1% for placebo, 1% for eptifibatide injection; p=0.029). Consistent with previous studies of GP IIb/IIIa inhibitors, most of the benefit achieved acutely with eptifibatide injection was in the reduction of MI. Eptifibatide injection reduced the occurrence of MI at 48 hours from 9% for placebo to 5.4% (p=0.0015) and maintained that effect with significance at 30 days.

There was no treatment difference with respect to sex in ESPRIT. Eptifibatide injection reduced the incidence of the primary endpoint in both men (95% confidence limits for relative risk: 0.54, 1.07) and women (0.24, 0.72) at 48 hours.

Follow-up (12-month) mortality data were available for 2024 patients (1017 on eptifibatide injection) enrolled in the ESPRIT trial (98.1% of the initial enrollment). Twelve-month clinical event data were available for 1964 patients (988 on eptifibatide injection), representing 95.2% of the initial enrollment. As shown in Table 9, the treatment effect of eptifibatide injection seen at 48 hours and 30 days appeared preserved at 6 months and 1 year. Most of the benefit was in reduction of MI.

Table 9. Clinical Events at 6 Months and 1 Year in the ESPRIT Study
 | Placebo (n=1024) | EptifibatideInjection; (n=1040) | Hazard Ratio; (95% CI)
Death, MI, or Target Vessel Revascularization
6 months | 187 (18.5%) | 146 (14.3%) | 0.744 (0.599, 0.924)
1 year | 222 (22.1%) | 178 (17.5%) | 0.762 (0.626, 0.929)
Death, MI
6 months | 117 (11.5%) | 77 (7.4%) | 0.631 (0.473, 0.841)
1 year | 126 (12.4%) | 83 (8%) | 0.63 (0.478, 0.832)
Percentages are Kaplan-Meier event rates.

16 HOW SUPPLIED/STORAGE AND HANDLING

16.1 How Supplied

Eptifibatide injection is supplied as a sterile solution in 10 mL vials containing 20 mg of eptifibatide (NDC 70436-162-80) and 100 mL vials containing 75 mg of eptifibatide (NDC 70436-163-80).

16.2 Storage

Vials should be stored refrigerated at 2° to 8°C (36° to 46°F). Vials may be transferred to room temperature storage* for a period not to exceed 2 months. Upon transfer, vial cartons must be marked by the dispensing pharmacist with a “DISCARD BY” date (2 months from the transfer date or the labeled expiration date, whichever comes first).

Protect from light until administration.

*Store at 25°C (77°F); excursions permitted to 15° to 30°C (59° to 86°F) [see USP Controlled Room Temperature].

17 PATIENT COUNSELING INFORMATION

Advise the patient to inform the doctor or healthcare provider about any medical conditions, medications, and allergies.

Rx only

PREMIERProRx® is a registered trademark of Premier Healthcare Alliance, L.P., used under license.

Manufactured by:

Hainan Poly Pharm. Co., Ltd.
Guilinyang Economic Development Area, Haikou, Hainan Province, China 571127

Distributed by:

Slate Run Pharmaceuticals, LLC

Columbus, Ohio 43215

10000233/02

Revised: 04/2021

PRINCIPAL DISPLAY PANEL - 20 mg CARTON LABEL

NDC 70436-162-80

Eptifibatide Injection, 20 mg/10 mL (2 mg/mL)

PRINCIPAL DISPLAY PANEL - 75 mg CARTON LABEL

NDC 70436-163-80

Eptifibatide Injection, 75 mg/100 mL (0.75 mg/mL)